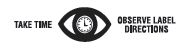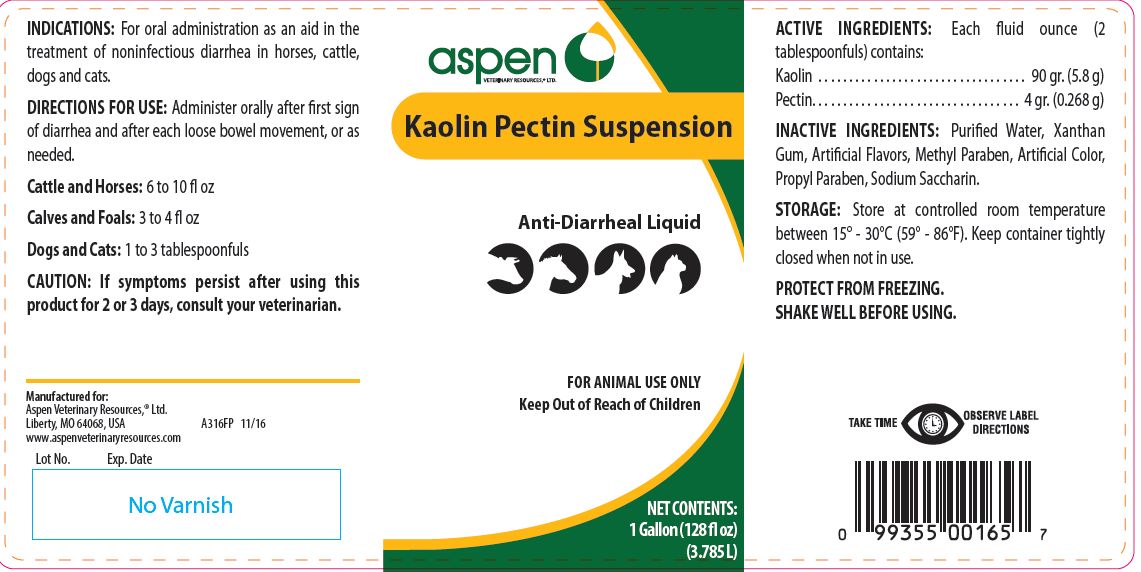 DRUG LABEL: Kaolin Pectin
NDC: 46066-233 | Form: SUSPENSION
Manufacturer: Aspen Veterinary
Category: animal | Type: OTC ANIMAL DRUG LABEL
Date: 20210126

ACTIVE INGREDIENTS: KAOLIN 208.1 g/1 L; PECTIN, CITRUS 8.8 g/1 L

Kaolin Pectin Suspension

PURPOSE

Anti-Diarrheal Liquid

KEEP OUT OF REACH OF CHILDREN

FOR ANIMAL USE ONLY
Keep Out of Reach of Children

INDICATIONS:

For oral administration as an aid in the treatment of noninfectious diarrhea in horses, cattle, dogs and cats.

DIRECTIONS FOR USE:

Administer orally after first sign of diarrhea and after each loose bowel movement, or as needed.
Cattle and Horses: 6 to 10 fl oz
Calves and Foals: 3 to 4 fl oz
Dogs and Cats: 1 to 3 tablespoonfuls

CAUTION:

If symptoms persist after using this product for 2 or 3 days, consult a veterinarian.

ACTIVE INGREDIENTS:

Each fluid ounce (2 tablespoonfuls) contains:
Kaolin . . . . . . . . . . . . . . . . . . . . . . . . . . . . . . . . . . 90 gr. (5.8 g)
Pectin. . . . . . . . . . . . . . . . . . . . . . . . . . . . . . . . . . 4 gr. (0.268 g)

INACTIVE INGREDIENTS:

Purified Water, Xanthan Gum, Artificial Flavors, Methyl Paraben, Artificial Color, Propyl Paraben, Sodium Saccharin.

STORAGE:

Store at controlled room temperature between 15° - 30°C (59° - 86°F). Keep container tightly closed when not in use.
PROTECT FROM FREEZING.
SHAKE WELL BEFORE USING.

NET CONTENTS:

32 FL OZ (946.35 mL)

1 Gallon (128 fl oz) (3.785 L)

INFORMATION FOR OWNERS/CAREGIVERS

Manufactured for:
Aspen Veterinary Resources,® Ltd.
Liberty, MO 64068, USA
www.aspenveterinaryresources.com